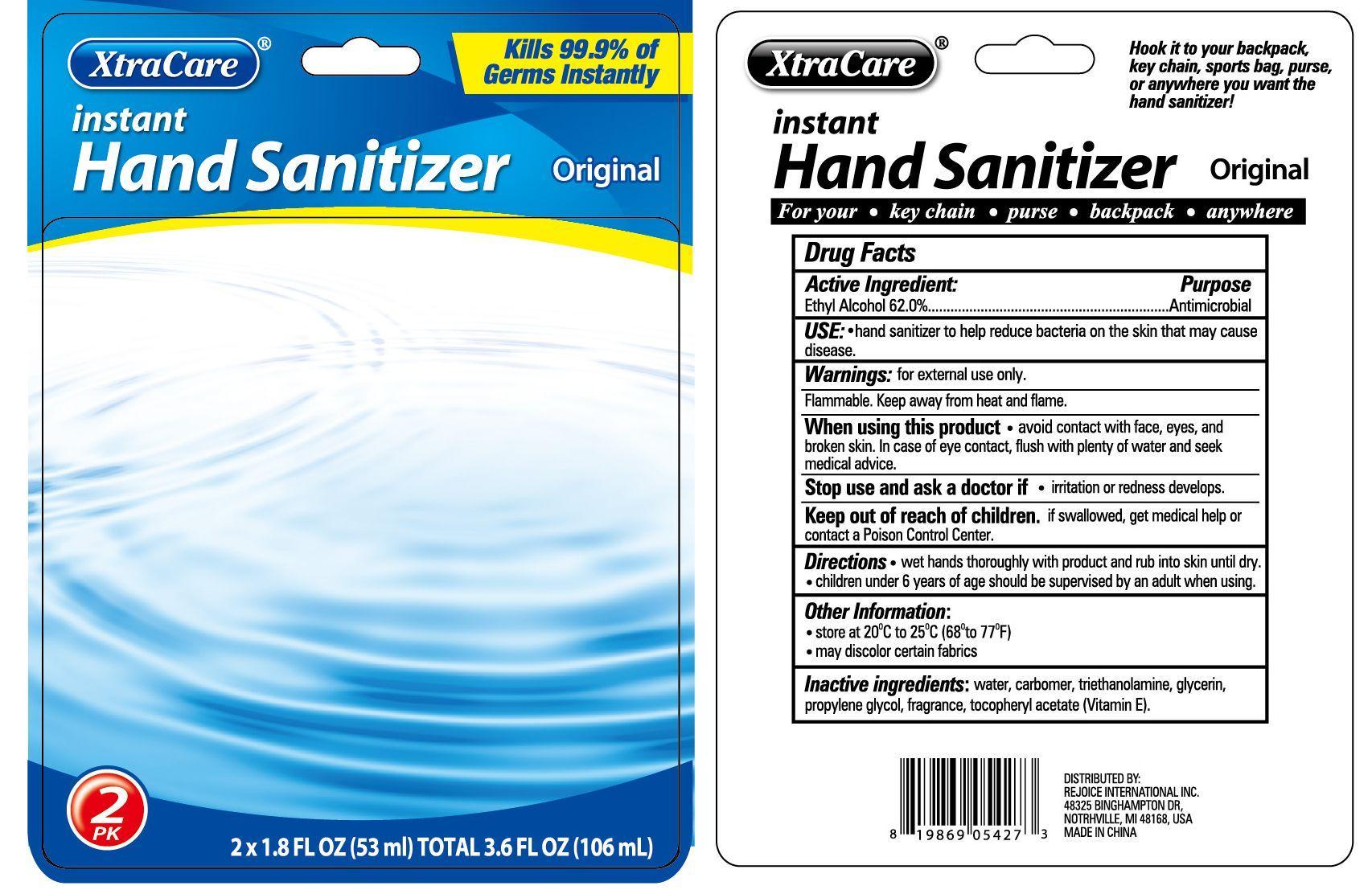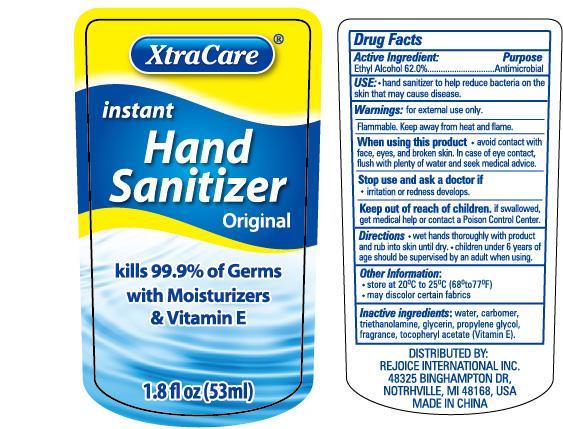 DRUG LABEL: Instant Hand Sanitizer - Original
NDC: 57337-017 | Form: GEL
Manufacturer: Rejoice International, Inc.
Category: otc | Type: HUMAN OTC DRUG LABEL
Date: 20240228

ACTIVE INGREDIENTS: ALCOHOL 33 mL/53 mL
INACTIVE INGREDIENTS: WATER; CARBOMER HOMOPOLYMER TYPE B; TROLAMINE; GLYCERIN; PROPYLENE GLYCOL; .ALPHA.-TOCOPHEROL ACETATE

Instant Hand Sanitizer - Original

Active Ingredient Purpose

Ethyl Alcohol 62.0%......................Antimicrobial

PURPOSE

XtraCare Instant Hand Sanitizer - Original

Kills 99.9% of Germs with Moisturizers & Vitamin E

Keep out of reach of children. If swallowed, get medical help or contact a Poison Control Center right away.

USE:

- hand sanitizer to help reduce bacteria on the skin that may cause disease

Warnings:

for external use only.

Flammable. Keep away from heat and flame.

Do not use in the eyes. In case of contact, rinse eyes thoroughly with water.

Stop use and ask a doctor if irritation and redness develop and persist for more than 72 hours.

Directions:

- wet hands thoroughly with product
- briskly rub hands together until dry
- children under 6 years of age should be supervised by an adult when using.

Inactive ingredients:

carbomer, glycerin, propylene glycol, tocopheryl acetate (vitamin E), triethanolamine, water, fragrance.